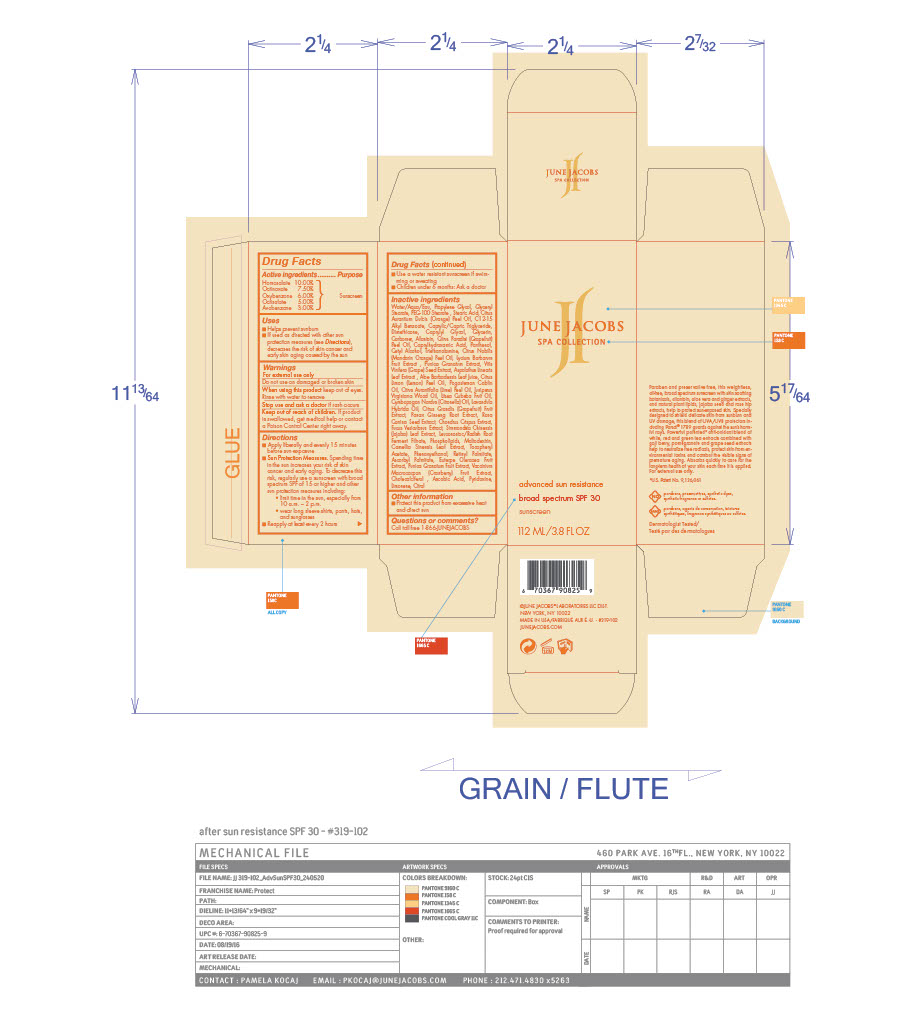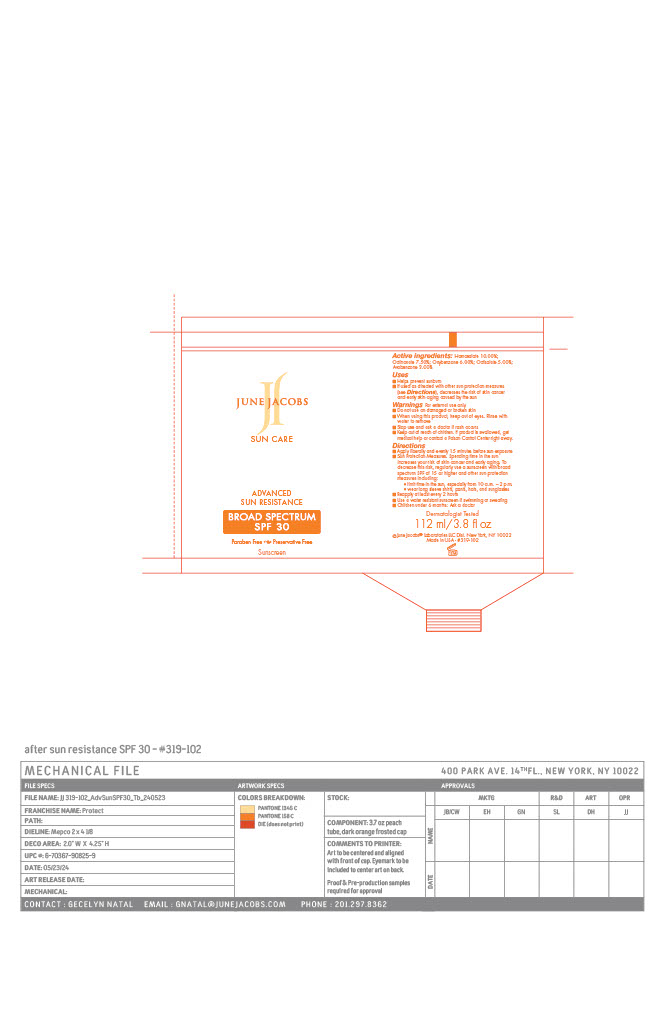 DRUG LABEL: Advanced Sun Resistance SPF 30
NDC: 65278-319 | Form: CREAM
Manufacturer: June Jacobs Labs, LLC
Category: otc | Type: HUMAN OTC DRUG LABEL
Date: 20240521

ACTIVE INGREDIENTS: AVOBENZONE 3.371 g/112.38 g; OXYBENZONE 6.743 g/112.38 g; OCTINOXATE 8.429 g/112.38 g; HOMOSALATE 11.238 g/112.38 g; OCTISALATE 5.619 g/112.38 g
INACTIVE INGREDIENTS: LEMON OIL; LAVANDIN OIL; ROSA CANINA SEED; LYCIUM BARBARUM FRUIT; CHONDRUS CRISPUS CARRAGEENAN; FUCUS VESICULOSUS; WATER; TROLAMINE; ASPALATHUS LINEARIS LEAF; ASIAN GINSENG; SOYBEAN LECITHIN; .ALPHA.-TOCOPHEROL ACETATE; ASCORBIC ACID; CHOLECALCIFEROL; PUNICA GRANATUM ROOT BARK; VITIS VINIFERA SEED; ALOE VERA LEAF; POGOSTEMON CABLIN LEAF OIL; PUMMELO; PEG-100 STEARATE; PROPYLENE GLYCOL; ALLANTOIN; MANDARIN OIL; LIME PEEL; PYRIDOXINE; DIMETHICONE; GLYCERIN; CARBOMER HOMOPOLYMER, UNSPECIFIED TYPE; JUNIPERUS VIRGINIANA OIL; LITSEA OIL; GLYCERYL MONOSTEARATE; STEARIC ACID; ALKYL (C12-15) BENZOATE; MEDIUM-CHAIN TRIGLYCERIDES; CAPRYLYL GLYCOL; GRAPEFRUIT OIL; GREEN TEA LEAF; PHENOXYETHANOL; LIMONENE, (+)-; ACAI; CRANBERRY; CAPRYLHYDROXAMIC ACID; CITRONELLA OIL; ORANGE OIL; PANTHENOL; CETYL ALCOHOL; SIMMONDSIA CHINENSIS LEAF; MALTODEXTRIN; VITAMIN A PALMITATE; ASCORBYL PALMITATE; CITRAL; LEUCONOSTOC/RADISH ROOT FERMENT FILTRATE; POMEGRANATE

Advanced Sun Resistance SPF 30

Active ingredients

Homosalate 10.00%

Octinoxate 7.50%

Oxybenzone 6.00%

Octisalate 5.00%

Avobenzone 3.00%

PURPOSE

Sunscreen

USES

■ Helps prevent sunburn

■ If used as directed with other sun protection measures (see Directions), decreases the risk of skin cancer and early skin aging caused by the sun

Warnings

For external use only

Do not use on damaged or broken skin

When using this product keep out of eyes. Rinse with water to remove

Stop use and ask a doctor if rash occurs

Keep out of reach of children. If product is swallowed, get medical help or contact a Poison Control Center right away

DOSAGE AND ADMINISTRATION

■ Apply liberally and evenly 15 minutes before sun exposure ■ Sun Protection Measures. Spending time in the sun increases your risk of skin cancer and early aging. To decrease this risk, regularly use a sunscreen with broad spectrum SPF of 15 or higher and other sun protection measures including:

• limit time in the sun, especially from 10 a.m. – 2 p.m.

• wear long sleeve shirts, pants, hats, and sunglasses

■ Reapply at least every 2 hours

■ Use a water resistant sunscreen if swim ming or sweating

■ Children under 6 months: Ask a doctor

Inactive ingredients

Water/Aqua/Eau, Propylene Glycol, Glyceryl Stearate, PEG-100 Stearate , Stearic Acid, Citrus Aurantium Dulcis (Orange) Peel Oil, C12-15 Alkyl Benzoate, Caprylic/Capric Triglyceride, Dimethicone, Caprylyl Glycol, Glycerin, Carbomer, Allantoin, Citrus Paradisi (Grapefruit) Peel Oil, Caprylhydroxamic Acid, Panthenol, Cetyl Alcohol, Triethanolamine, Citrus Nobilis (Mandarin Orange) Peel Oil, Lycium Barbarum Fruit Extract , Punica Granatum Extract, Vitis Vinifera (Grape) Seed Extract, Aspalathus Linearis Leaf Extract , Aloe Barbadensis Leaf Juice, Citrus Limon (Lemon) Peel Oil, Pogostemon Cablin Oil, Citrus Aurantifolia (Lime) Peel Oil, Juniperus Virginiana Wood Oil, Litsea Cubeba Fruit Oil, Cymbopogon Nardus (Citronella) Oil, Lavandula Hybrida Oil, Citrus Grandis (Grapefruit) Fruit Extract, Panax Ginseng Root Extract, Rosa Canina Seed Extract, Chondrus Crispus Extract, Fucus Vesiculosus Extract, Simmondsia Chinensis (Jojoba) Leaf Extract, Leuconostoc/Radish Root Ferment Filtrate, Phospholipids, Maltodextrin, Camellia Sinensis Leaf Extract, Tocopheryl Acetate, Phenoxyethanol, Retinyl Palmitate, Ascorbyl Palmitate, Euterpe Oleracea Fruit Extract, Punica Granatum Fruit Extract, Vaccinium Macrocarpon (Cranberry) Fruit Extract, Cholecalciferol , Ascobic Acid, Pyridoxine, Limonene, Citral

Other information

■ Protect this product from excessive heat and direct sun

Questions or comments?

Call toll free 1-866-JUNEJACOBS